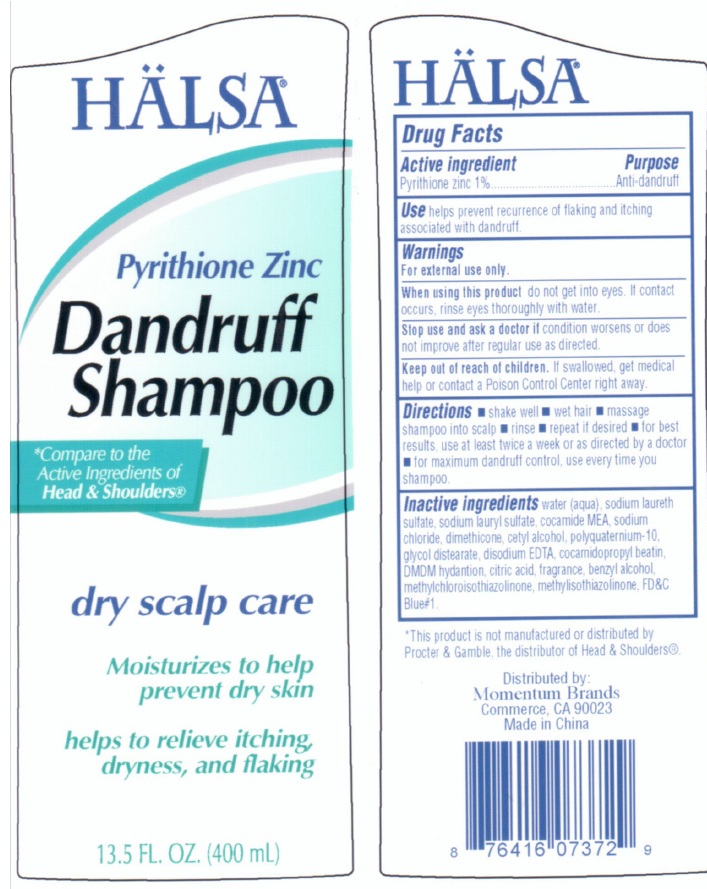 DRUG LABEL: Halsa Pyrithione Zinc Dandruff - Dry Scalp Care
NDC: 75884-200 | Form: SHAMPOO
Manufacturer: Momentum Brands dba 99 Cents Only Stores
Category: otc | Type: HUMAN OTC DRUG LABEL
Date: 20110107

ACTIVE INGREDIENTS: PYRITHIONE ZINC 1 mL/100 mL
INACTIVE INGREDIENTS: WATER; SODIUM LAURETH SULFATE; SODIUM LAURYL SULFATE; COCO MONOETHANOLAMIDE; SODIUM CHLORIDE; DIMETHICONE; CETYL ALCOHOL; POLYQUATERNIUM-10 (400 CPS AT 2%); GLYCOL DISTEARATE; EDETATE DISODIUM; COCAMIDOPROPYL BETAINE; DMDM HYDANTOIN; CITRIC ACID MONOHYDRATE; BENZYL ALCOHOL; METHYLCHLOROISOTHIAZOLINONE; METHYLISOTHIAZOLINONE; FD&C BLUE NO. 1

Halsa Pyrithione Zinc Dandruff Shampoo - Dry Scalp Care

Active Ingredient Purpose

Pyrithione Zinc 1% Anti-dandruff

Purpose

Anti-dandruff

INDICATIONS AND USAGE

Use helps prevent recurrence of flaking and itching associated with dandruff.

Warnings

For external use only.

When using this product do not get into eyes. If contact occurs, rinse eyes thoroughly with water.

Stop use and ask a doctor if condition worsens or does not improve after regular use as directed.

Keep out of reach of children. If swallowed, get medical help or contact a Poison Control Center right away.

Directions

Shake well

wet hair

massage shampoo into scalp

rinse

repeat if desired

for best results, use at least twice a week or as directed by a doctor

for maximum dandruff control, use every time you shampoo.

Inactive Ingredients

water (aqua), sodium laureth sulfate, sodium lauryl sulfate, cocamide MEA, sodium chloride, dimethicone, cetyl alcohol, polyquaternium-10, glycol distearate, disodium EDTA, cocamidopropyl betain, DMDM hydantoin, citric acid, fragrance, benzyl alcohol, methylchloroisothiazolinone, methylisothiazolinone, FD and C Blue 1

DESCRIPTION

This product is not manufactured or distributed by

Procter and Gamble, the distributor of Head and Shoulders

Manufactured in China

Exclusively for and Distributed by:

Personal Care Products, Inc.

Bingham Farms, MI 48025-2463

PACKAGE LABEL

Halsa

Pyrithione Zinc

Dandruff

Shampoo

Compare to the

Active Ingredients of

Head and Shoulders

dry scalp care

moisturizes to help prevent dry skin

helps to relieve itching dryness and flaking.

13.5 FL. OZ. (400 mL)